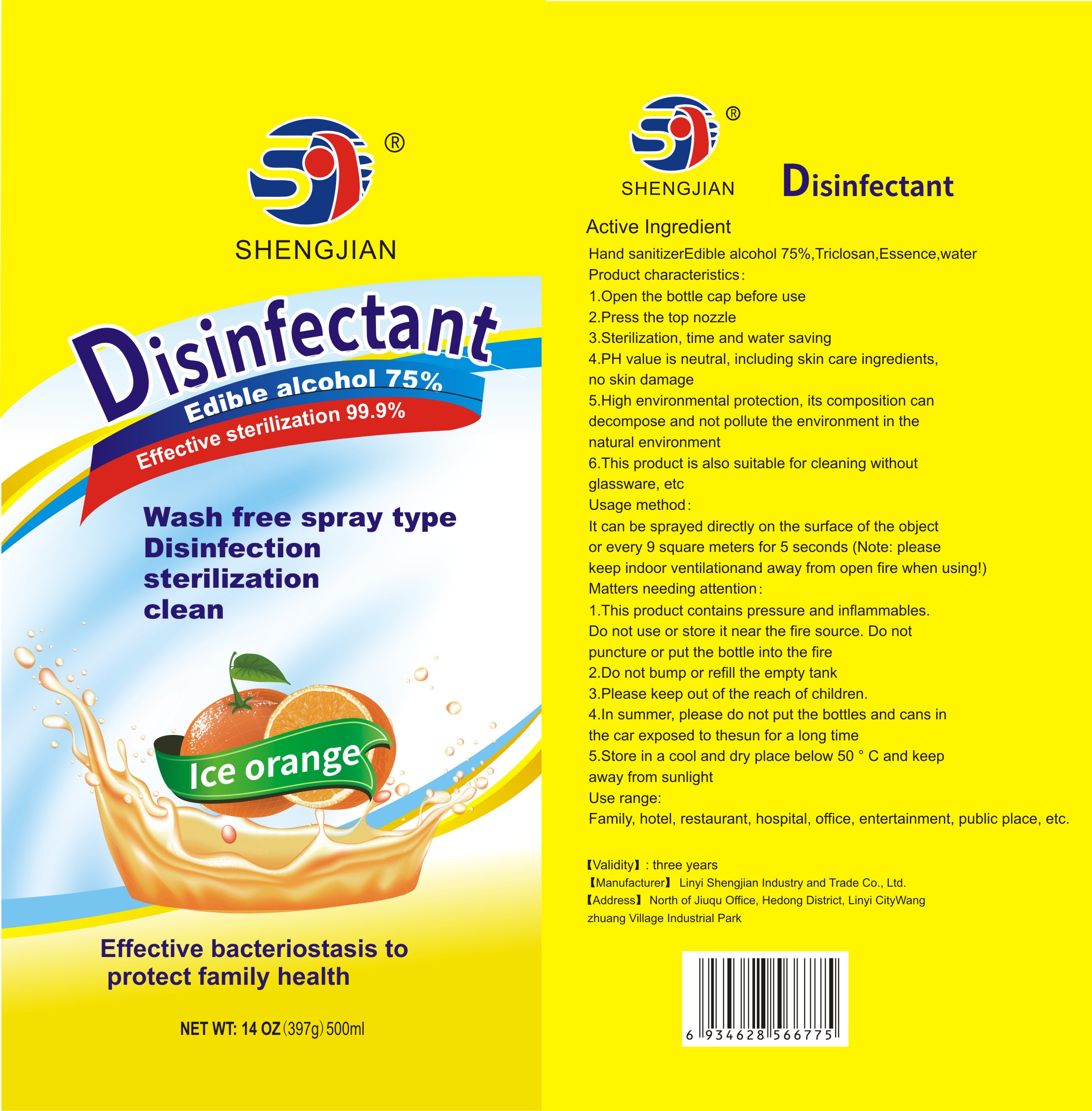 DRUG LABEL: Disinfectant
NDC: 78024-001 | Form: SPRAY
Manufacturer: LINYI SHENGJIAN INDUSTRY & TRADE CO., LTD
Category: otc | Type: HUMAN OTC DRUG LABEL
Date: 20200519

ACTIVE INGREDIENTS: ALCOHOL 75 mL/100 mL
INACTIVE INGREDIENTS: METHYL BENZOATE; WATER; TRICLOSAN

Disinfectant

Active Ingredient(s)

Edible alcohol 75%.

Purpose

Disinfection.sterilization,clean

Usage method

It can be sprayed directly on the surface of the object

or every 9 square meters for 5 seconds(Note：please

keep indoor ventilation and away from open fire when using!)

Warnings

This product contains pressure and inflammables.

Do not puncture or put the bottle into the fire.

Do not use or store it near the fire source.

WHEN USING

1.Open the bottle cap before use

2.Press the top nozzle

3.Sterilization, time and water saving

4.PH value is neutral, including skin care ingredients,no skin damage

5.High environmental protection, its composition can decompose and not pollute the environment in the natural environment

6.This product is also suitable for cleaning without glassware,etc

Please keep out of reach of the children.

Other information

- In summer, please do not put the bottles and cans in the car exposed to the sun for a long time
- Store in a cool and dry place below 50℃ and keep away from sunlight.

Inactive ingredients

Triclosan, Essence, water